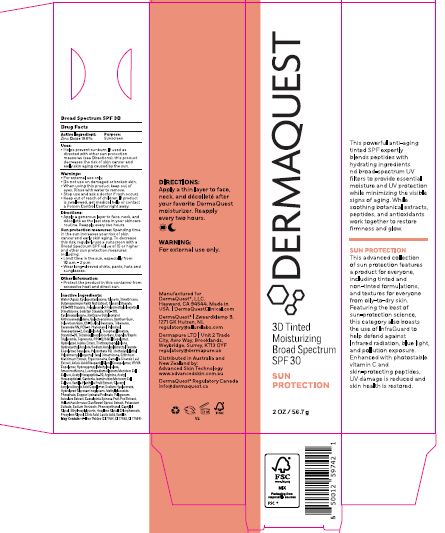 DRUG LABEL: 3D Tinted Moisturizing BS SPF 30
NDC: 62742-4277 | Form: CREAM
Manufacturer: Allure Labs
Category: otc | Type: HUMAN OTC DRUG LABEL
Date: 20260109

ACTIVE INGREDIENTS: ZINC OXIDE 18.6 g/100 g
INACTIVE INGREDIENTS: BUTYROSPERMUM PARKII (SHEA) BUTTER; PEG-10; STEARETH-20; TETRAHEXYLDECYL ASCORBATE; NEOPENTYL GLYCOL; HELIANTHUS ANNUUS SPROUT; SODIUM BENZOATE; CAPRYLYL GLYCOL; PROPYLENE GLYCOL; WATER; PEG-100; HYDROXYETHYL ACRYLATE/SODIUM ACRYLOYLDIMETHYL TAURATE COPOLYMER (45000 MPA.S AT 1%); ACETYL HEXAPEPTIDE-38; VANILLA PLANIFOLIA FRUIT; HYDROLYZED GLYCOSAMINOGLYCANS (BOVINE; 50000 MW); COPPER LYSINATE; CAESALPINIA SPINOSA FRUIT POD; LACTIC ACID; VANILLIN; GLYCERYL STEARATE; CYCLOPENTASILOXANE; GALACTOARABINAN; SQUALANE; GLYCERYL ACRYLATE/ACRYLIC ACID COPOLYMER (300000 CP AT 2%); POTASSIUM SORBATE; GLYCERIN; POLYGLYCERYL-3 POLYDIMETHYLSILOXYETHYL DIMETHICONE (4000 MPA.S); SORBITAN STEARATE; CYCLOHEXASILOXANE; XANTHAN GUM; SCLEROTIUM GUM; TRIBEHENIN; CERAMIDE NG; PALMITOYL HEXAPEPTIDE-12; CAPRYLIC/CAPRIC TRIGLYCERIDE; TEPRENONE; PPG-12/SMDI COPOLYMER; HYDROLYZED JOJOBA ESTERS; TRIETHOXYCAPRYLYLSILANE; SODIUM ACRYLOYLDIMETHYLTAURATE; POLYSORBATE 60; CRITHMUM MARITIMUM; CAMELLIA SINENSIS LEAF; ADIPIC ACID; VP/VA COPOLYMER; AMODIMETHICONE (1300 CST); LEONTOPODIUM ALPINUM FLOWERING TOP; ARGININE; ACETYL HEXAPEPTIDE-8; GARDENIA JASMINOIDES FRUIT; SODIUM HYALURONATE; PROLINTANE; POLYGONUM AVICULARE TOP; PHENOXYETHANOL; ETHYLHEXYLGLYCERIN; HEXYLENE GLYCOL; CITRIC ACID; CI 77491; CI 77492; CI 77499; DIMETHICONE; PEG-100 STEARATE; C12-15 ALKYL BENZOATE; CETYL ALCOHOL; .ALPHA.-TOCOPHEROL ACETATE; TRIETHOXYSILYLETHYL POLYDIMETHYLSILOXYETHYL HEXYL DIMETHICONE; ERGOTHIONEINE; HYDROXYPROPYL METHYLCELLULOSE

Drug Facts

Active Ingredient: Zinc Oxide 18.6 %

Purpose :Sunscreen

INDICATIONS AND USAGE

Uses ■ helps prevent sunburn • if used as directed with other sun protection measures (see Directions), decreases the risk of skin cancer and early skin aging caused by the sun

Warnings • For external use only

Do not use on damaged or broken skin

When using this product keep out of eyes. Rinse with water to remove.

Stop use and ask a doctor if rash occurs

Keep out of reach of children. If swallowed, get medical help or contact a Poison Control Center right away.

Directions:

Apply a generous layer to face, neck , and decollate as the last step in your skincare routine. Reapply every two hours.

Sun Protection Measures. Spending time in the sun increases your risk of skin cancer and early skin aging. To decrease this risk, regularly use a sunscreen with a Broad Spectrum SPF value of 15 or higher and other sun protection measures including: • limit time in the sun, especially from 10 a.m.- 2 p.m. • wear long-sleeved shirts, pants, hats and sunglasses

Other information • protect the product in this container from excessive heat and direct sun

Inactive Ingredients
Water (Aqua) , Cyclopentasiloxane Glycerin, Dimethicone, Butyrospermum Parkii Nut Extract Glyceryl Stearate, PEG-100 Stearate, Polyglyceryl-3 Polydimethylsiloxyethyl Dimethicone, Sorbitan Stearate, PEG-100 ,Cyclohexasiloxane, Bis(Cyano Butylacetate) Anthracenediylidene, ,Galactoarabinan , Xanthan Gum, Sclerotium Gum, C12-15 Alkyl Benzoate, Tribehenin, Ceramide NG ,PEG-10 Phytosterol, Palmitoyl Hexapeptide-12, Cetyl Alcohol , Tocopheryl Acetate, Steareth-20, Tetrahexyldecyl Ascorbate, Caprylic/Capric Triglyceride, Teprenone,PPG-12/SMDI Copolymer, Hydrolyzed Jojoba Esters, Triethoxycaprylylsilane, Hydroxyethyl Acrylate/Sodium
Acryloyldimethyl Taurate Copolymer, Squalane, Polysorbate 60, Triethoxysilylethyl
Polydimethylsiloxyethyl Hexyl Dimethicone, Crithmum Maritimum Extract, Ergothioneine, Camellia Sinensis Leaf Extract, Adipic Acid/Neopentyl Glycol Crosspolymer, VP/VA Copolymer, Hydroxypropyl Methylcellulose, Amodimethicone, Leontopodium Alpinum Meristem Cell Culture, Acetyl Hexapeptide-30, Arginine, Acetyl Hexapeptide-8, Gardenia Jasminoides Meristem Cell Culture, Vanilla Planifolia Fruit Extract, Glyceryl Acrylate/Acrylic Acid Copolymer, Sodium Hyaluronate, Hydrolyzed Glycosaminoglycans, Methylglucoside Phosphate, Copper Lysinate/Prolinate, Polygonum Aviculare Extract, Caesalpinia Spinosa Fruit Pod Extract, Helianthus Annuus (Sunflower)Sprout Extract, Potassium Sorbate, Sodium Benzoate, Phenoxyethanol, Caprylyl Glycol, Ethylhexylglycerin, Hexylene Glycol, Hexylene Glycol, Propylene Glycol, Citric Acid, Lactic Acid, Vanillin, Iron Oxides (CI 77491, CI 77492, CI 77499)